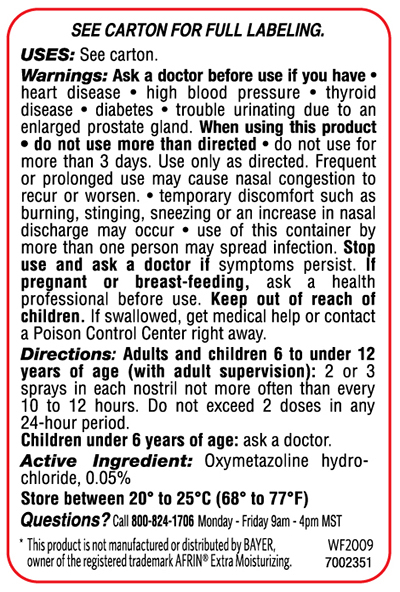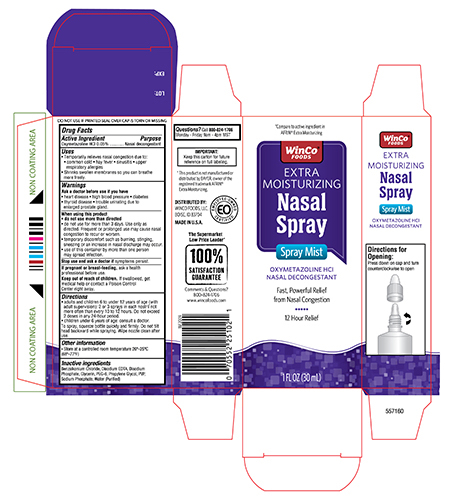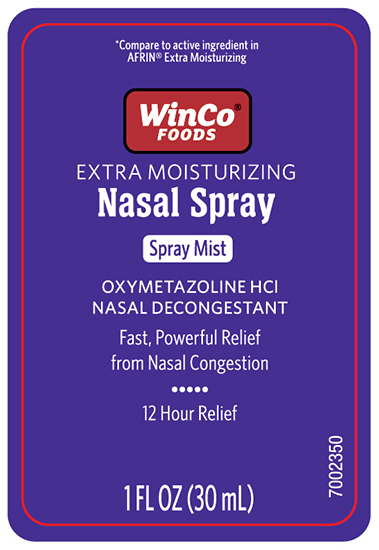 DRUG LABEL: 12 Hour Nasal Decongestant Extra Moisturizing
NDC: 67091-377 | Form: LIQUID
Manufacturer: WinCo Foods LLC
Category: otc | Type: HUMAN OTC DRUG LABEL
Date: 20241121

ACTIVE INGREDIENTS: OXYMETAZOLINE HYDROCHLORIDE 50 mg/100 mL
INACTIVE INGREDIENTS: POLYETHYLENE GLYCOL 300; GLYCERIN; PROPYLENE GLYCOL; DISODIUM EDTA-COPPER; SODIUM PHOSPHATE, MONOBASIC; SODIUM PHOSPHATE, DIBASIC, ANHYDROUS; POVIDONE K29/32; BENZALKONIUM CHLORIDE; WATER

Winco 12 Hour Nasal Spray Extra Moisturizing

Drug Facts

Active Ingredient
Oxymetazoline Hydrochloride 0.05%

Purpose

Nasal Decongestant

Uses

Temporarily relieves nasal congestion due to:

- common cold
- hay fever
- sinusitis
- upper respirtory allergies
- Shrink swollen membranes so you can breathe more freely

Ask a Doctor before use if you have

- heart diease
- high blood pressure
- diabetes
- thyiod diease
- trouble urinating due to enlarged rostate gland.

When using this product

- Do not use more than directed
- do not use for more than three days, Use only as directed. Frequent or prolonged use may cause nasal congestion to recur or worsen.
- temporary discomfort such as burning ,stinging, sneezing or an increase in nasal discharge may occur
- use of this container by more thna one person may spread infection.

stop use and ask a doctor if

symptoms persist.

PREGNANCY

ask a health professional before use.

Keep out of the reach of children

if swallowed, get medical help or contact a Poison Control Center right away.

DOSAGE AND ADMINISTRATION

- Adults and children 6 to under 12 years of age (with adult supervision):2 or 3 sprays in each nostril not more than every 10 to 12 hours. Do not exceed 2 doses in any 24-hour period.
- Children under 6 years of age consult a doctor.To spray, squeeze bottle quickly and firmly. Do not tilt head backwards while spraying, wipe nozzle clean after use.

Other information

- store between 20° and 25°C (68° to 77°F)
- retain carton for future reference on full labeling

Inactive Ingredients:

benzalkonium chloride, edetate disodium, glycerin, polyethylene glycol, povidone, propylene glycol, sodium phosphate dibasic, sodium phosphate monobasic, water

Principal display panel- Carton

WinCo Foods

Extra Moisturizing Nasal Spray

Oxymetazoline HCL 0.05%

Fast Powerful relief of Nasal congestion

12 Hour Relief

1 FL OZ (30ml)

Principal display panel -Bottle label Front

WinCo Foods

Extra Moisturizing Nasal Spray

Oxymetazoline HCL 0.05%

Fast Powerful Relief of Nasal congestion

12 Hour Relief

1 FL OZ (30ml)